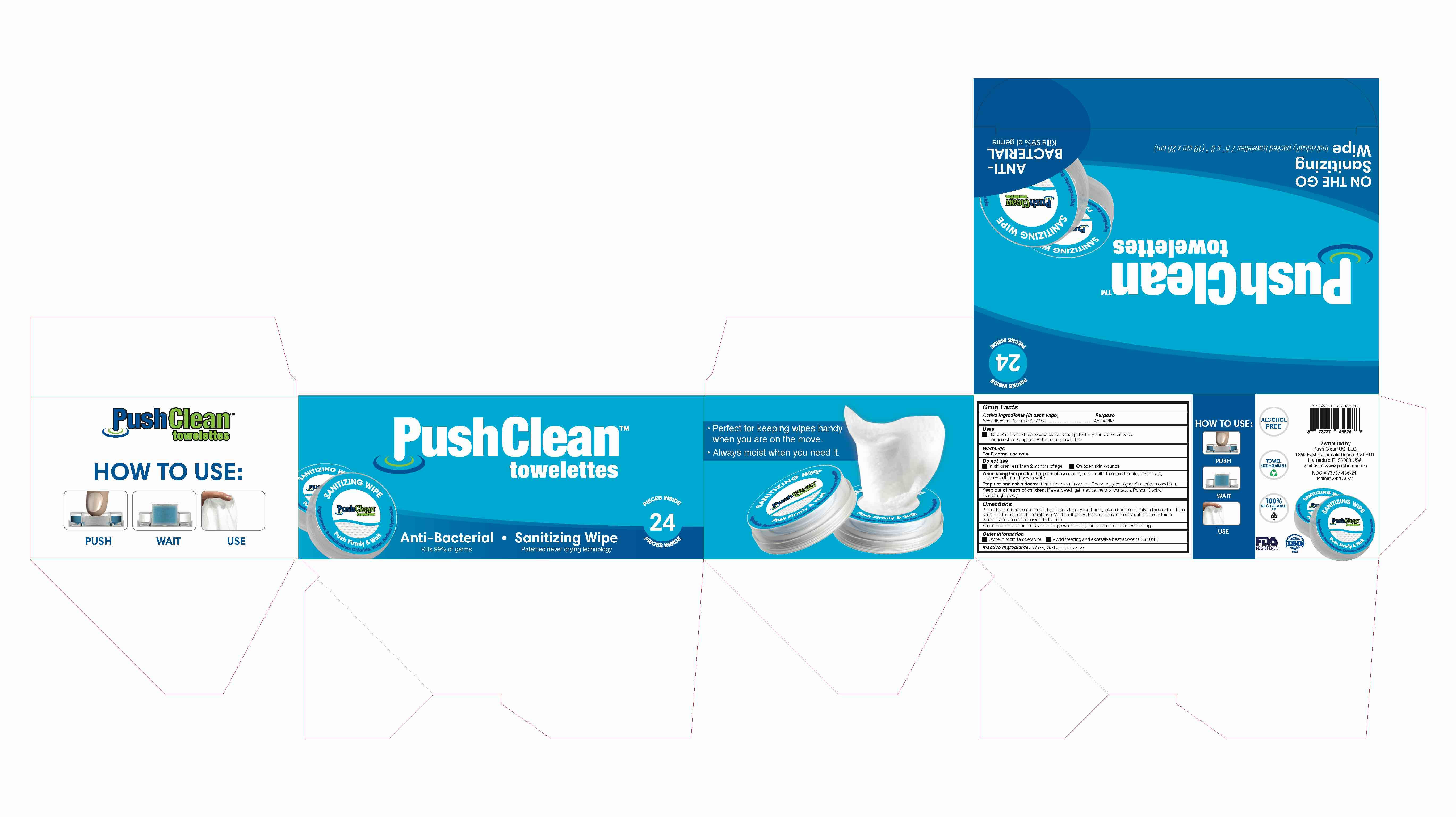 DRUG LABEL: Push Clean
NDC: 73737-436 | Form: CLOTH
Manufacturer: pushclean technology plastik sanayi ve ticaret limited sirketi
Category: otc | Type: HUMAN OTC DRUG LABEL
Date: 20241024

ACTIVE INGREDIENTS: BENZALKONIUM CHLORIDE 1.3 mg/1 mL
INACTIVE INGREDIENTS: WATER; SODIUM HYDROXIDE

Hand Sanitizer Wipes

Active Ingredient (in each wipe)

Benzalkonium Chloride 0.13% Purpose: Antiseptic

Purpose

Antiseptic

Use[s]

Hand Sanitizer to help reduce bacteria that potentially can cause disease. For use when soap and water are not available.

Warnings

For external use only

Do not use

- in children less than 2 months of age
- on open skin wounds

Stop use and ask a doctor

if irritation or rash occurs. These may be signs of a serious condition.

Keep out of reach of children

If swallowed, get medical help or contact a Poison Control Center right away

Directions

- Place the container on a hard flat surface. Using your thumb, press and hold firmly in the center of the container for a second and release. Wait for the towelette to rise completely out of the container. Remove and unfold the towelette for use.
- Supervise children under 6 years of age when using this product to avoid swallowing.

Other information

- Avoid freezing and excessive heat above 40C (104F)
- Store between 20-25 C (68-77F)

Inactive ingredients

sodium hydroxide, water

PACKAGE LABEL

73737-436-24